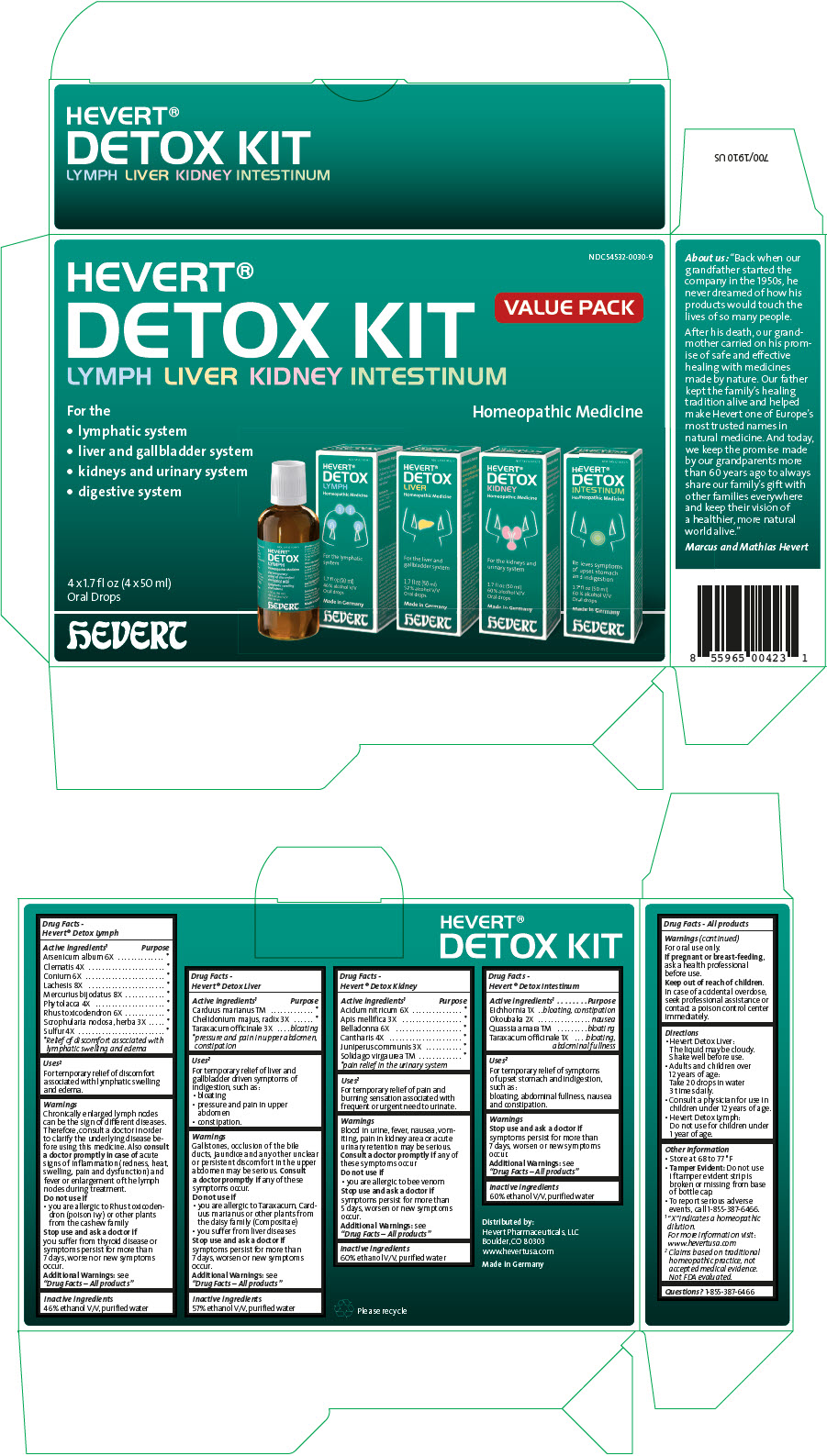 DRUG LABEL: HEVERT DETOX
NDC: 54532-0030 | Form: KIT | Route: ORAL
Manufacturer: Hevert Arzneimittel GmbH & Co KG
Category: homeopathic | Type: HUMAN OTC DRUG LABEL
Date: 20221215

ACTIVE INGREDIENTS: Arsenic Trioxide 6 [hp_X]/50 mL; Clematis Recta Flowering top 4 [hp_X]/50 mL; Conium Maculatum Flowering Top 6 [hp_X]/50 mL; Lachesis Muta Venom 8 [hp_X]/50 mL; Mercuric Iodide 8 [hp_X]/50 mL; Phytolacca Americana Root 4 [hp_X]/50 mL; Toxicodendron Pubescens shoot 6 [hp_X]/50 mL; Scrophularia Nodosa leaf with stem 3 [hp_X]/50 mL; Sulfur 4 [hp_X]/50 mL; Milk Thistle 1 [hp_X]/50 mL; Chelidonium majus root 3 [hp_X]/50 mL; Taraxacum officinale 3 [hp_X]/50 mL; Nitric Acid 6 [hp_X]/50 mL; Apis Mellifera 3 [hp_X]/50 mL; Atropa Belladonna 6 [hp_X]/50 mL; Lytta Vesicatoria 4 [hp_X]/50 mL; Juniper Berry 3 [hp_X]/50 mL; Solidago Virgaurea Flowering Top 1 [hp_X]/50 mL; Eichhornia Crassipes Whole 1 [hp_X]/50 mL; Okoubaka aubrevillei bark 2 [hp_X]/50 mL; QUASSIA AMARA WOOD 1 [hp_X]/50 mL; TARAXACUM OFFICINALE 1 [hp_X]/50 mL
INACTIVE INGREDIENTS: Alcohol; Water; Alcohol; Water; Alcohol; Water; Alcohol; Water

HEVERT DETOX KIT

Drug Facts - Hevert® Detox Lymph

ACTIVE INGREDIENT

PURPOSE

Active ingredients ["X" indicates a homeopathic dilution. For more information visit: www.hevertusa.com] | Purpose
Arsenicum album 6X | [Relief of discomfort associated with lymphatic swelling and edema]
Clematis 4X
Conium 6X
Lachesis 8X
Mercurius bijodatus 8X
Phytolacca 4X
Rhus toxicodendron 6X
Scrophularia nodosa, herba 3X
Sulfur 4X

Uses [Claims based on traditional homeopathic practice, not accepted medical evidence. Not FDA evaluated.]

For temporary relief of discomfort associated with lymphatic swelling and edema.

Warnings

Chronically enlarged lymph nodes can be the sign of different diseases. Therefore, consult a doctor in order to clarify the underlying disease before using this medicine. Also consult a doctor promptly in case of acute signs of inflammation (redness, heat, swelling, pain and dysfunction) and fever or enlargement of the lymph nodes during treatment.

Do not use if

- you are allergic to Rhus toxicodendron (poison ivy) or other plants from the cashew family

Stop use and ask a doctor if you suffer from thyroid disease or symptoms persist for more than 7 days, worsen or new symptoms occur.

Additional Warnings

see "Drug Facts – All products"

Inactive ingredients

46% ethanol V/V, purified water

Drug Facts - Hevert® Detox Liver

ACTIVE INGREDIENT

PURPOSE

Active ingredients ["X" indicates a homeopathic dilution. For more information visit: www.hevertusa.com] | Purpose
Carduus marianus TM | [pressure and pain in upper abdomen, constipation]
Chelidonium majus, radix 3X
Taraxacum officinale 3X | bloating

Uses [Claims based on traditional homeopathic practice, not accepted medical evidence. Not FDA evaluated.]

For temporary relief of liver and gallbladder driven symptoms of indigestion, such as:

- bloating
- pressure and pain in upper abdomen
- constipation.

Warnings

Gallstones, occlusion of the bile ducts, jaundice and any other unclear or persistent discomfort in the upper abdomen may be serious. Consult a doctor promptly if any of these symptoms occur.

Do not use if

- you are allergic to Taraxacum, Carduus marianus or other plants from the daisy family (Compositae)
- you suffer from liver diseases

Stop use and ask a doctor if symptoms persist for more than 7 days, worsen or new symptoms occur.

Additional Warnings

see "Drug Facts – All products"

Inactive ingredients

57% ethanol V/V, purified water

Drug Facts - Hevert® Detox Kidney

ACTIVE INGREDIENT

PURPOSE

Active ingredients ["X" indicates a homeopathic dilution. For more information visit: www.hevertusa.com] | Purpose
Acidum nitricum 6X | [pain relief in the urinary system]
Apis mellifica 3X
Belladonna 6X
Cantharis 4X
Juniperus communis 3X
Solidago virgaurea TM

Uses [Claims based on traditional homeopathic practice, not accepted medical evidence. Not FDA evaluated.]

For temporary relief of pain and burning sensation associated with frequent or urgent need to urinate.

Warnings

Blood in urine, fever, nausea, vomiting, pain in kidney area or acute urinary retention may be serious. Consult a doctor promptly if any of these symptoms occur

Do not use if

- you are allergic to bee venom

Stop use and ask a doctor if symptoms persist for more than 5 days, worsen or new symptoms occur.

Additional Warnings

see "Drug Facts – All products"

Inactive ingredients

60% ethanol V/V, purified water

Drug Facts - Hevert® Detox Intestinum

ACTIVE INGREDIENT

PURPOSE

Active ingredients ["X" indicates a homeopathic dilution. For more information visit: www.hevertusa.com] | Purpose
Eichhornia 1X | bloating, constipation
Okoubaka 2X | nausea
Quassia amara TM | bloating
Taraxacum officinale 1X | bloating, abdominal fullness

Uses [Claims based on traditional homeopathic practice, not accepted medical evidence. Not FDA evaluated.]

For temporary relief of symptoms of upset stomach and indigestion, such as:

bloating, abdominal fullness, nausea and constipation.

Warnings

Stop use and ask a doctor if symptoms persist for more than 7 days, worsen or new symptoms occur.

Additional Warnings

see "Drug Facts – All products"

Inactive ingredients

60% ethanol V/V, purified water

Drug Facts - All products

Warnings

For oral use only.

PREGNANCY OR BREAST FEEDING

If pregnant or breast-feeding, ask a health professional before use.

Keep out of reach of children. In case of accidental overdose, seek professional assistance or contact a poison control center immediately.

Directions

- Hevert Detox Liver:
  The liquid may be cloudy. Shake well before use.
- Adults and children over 12 years of age:
  Take 20 drops in water 3 times daily.
- Consult a physician for use in children under 12 years of age.
- Hevert Detox Lymph:
  Do not use for children under 1 year of age.

Other Information

- Store at 68 to 77 °F
- Tamper Evident: Do not use if tamper evident strip is broken or missing from base of bottle cap.
- To report serious adverse events, call 1-855-387-6466.

Questions?

1-855-387-6466

Distributed by:
Hevert Pharmaceuticals, LLC
Boulder, CO 80303

PRINCIPAL DISPLAY PANEL - Kit Carton

NDC 54532-0030-9

HEVERT®
DETOX KIT
LYMPH LIVER KIDNEY INTESTINUM

VALUE PACK

For the

- lymphatic system
- liver and gallbladder system
- kidneys and urinary system
- digestive system

Homeopathic Medicine

4 x 1.7 fl oz (4 x 50 ml)
Oral Drops

hEVERT